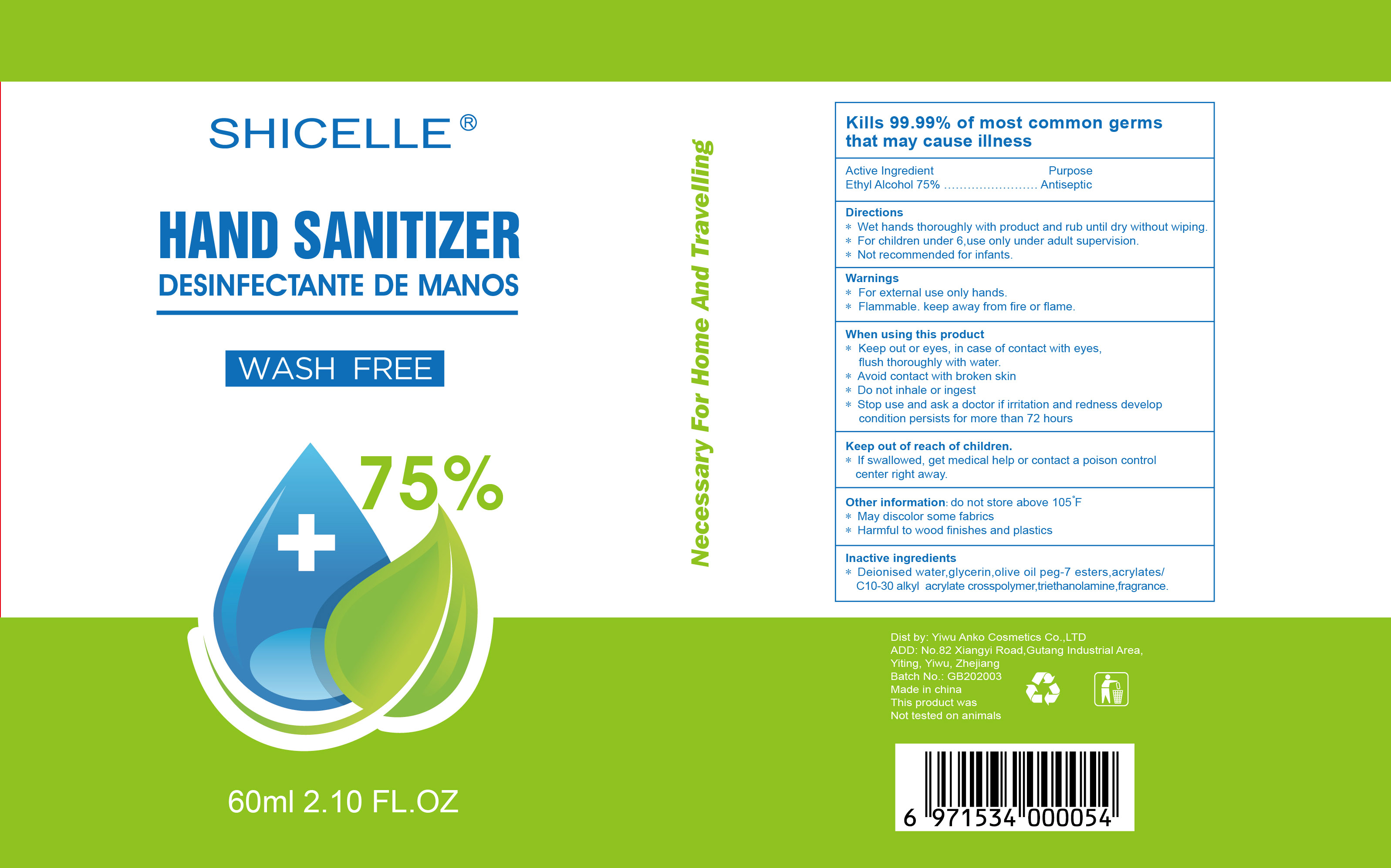 DRUG LABEL: SHICELLE Hand Sanitizer
NDC: 77292-001 | Form: SOLUTION
Manufacturer: YIWU ANKO COSMETICS CO., LTD
Category: otc | Type: HUMAN OTC DRUG LABEL
Date: 20200504

ACTIVE INGREDIENTS: ALCOHOL 75 mL/100 mL
INACTIVE INGREDIENTS: GLYCERIN; WATER; TROLAMINE

Active Ingredient(s)

Ethyl Alcohol 75% v/v

Purpose

Antiseptic

Use

To reduce bacteria on the skin that could cause disease

Recommended for repeated use

Warnings

For external use only -hands

Flammable. Keep away from fire or flame

When using this product keep out of eyes. In case of contact with eyes, flush thoroughly with water.

Avoid contact with broken skin

Do not inhale or ingest

Stop use and ask a doctor if irritation and redness develop and condistion persists for more than 72 hours

Keep out of reach of children. If swallowed, get medical help or contact a Poison Control Center right away

Directions

- Wet hands thoroughly with product and rub until dry without wiping
- For children under 6, use only under adult supervision
- Not recommended for infants

Other information

Do not store above 105F

May discolor some fabrics

Harmful to wood finishes and plastics

Inactive ingredients

Water, glycerin, olive oil PEG-7 ester, acrylates /C10-30 alkyl acrylate cross polymer, triethanolamine, fragrance